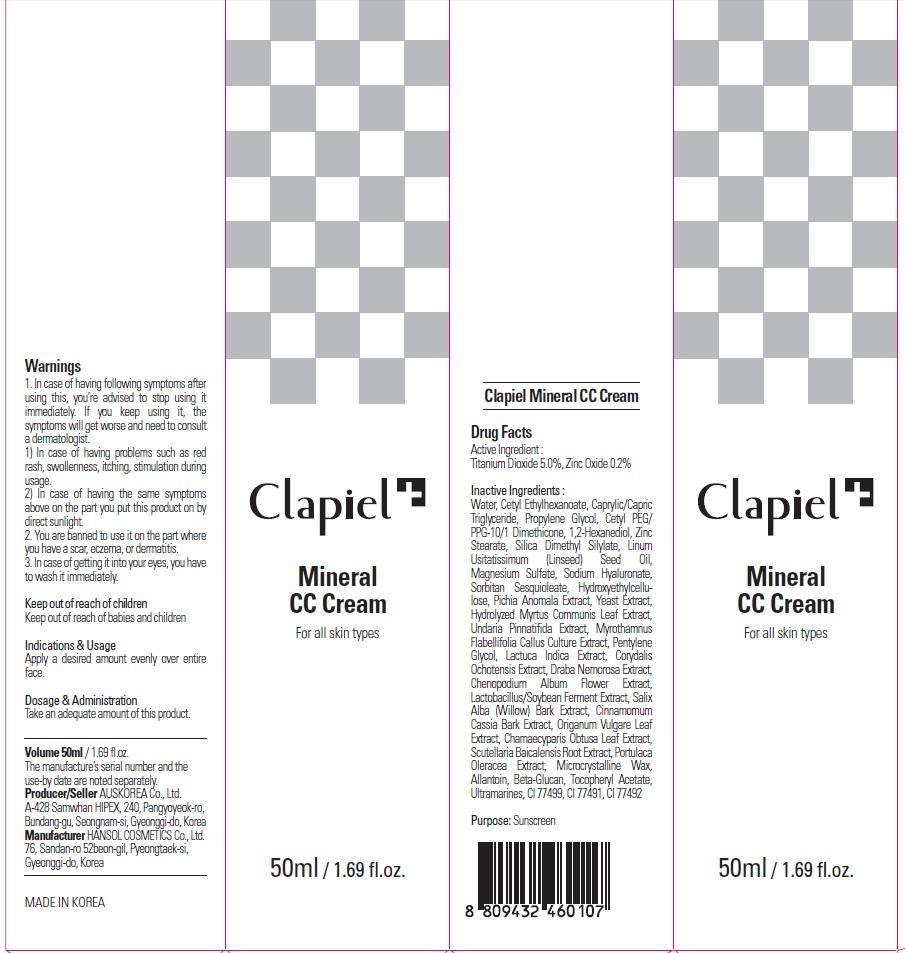 DRUG LABEL: Clapiel Mineral CC
NDC: 69977-030 | Form: CREAM
Manufacturer: AUS KOREA CO., LTD.
Category: otc | Type: HUMAN OTC DRUG LABEL
Date: 20150724

ACTIVE INGREDIENTS: Titanium Dioxide 2.5 mg/50 mL; Zinc Oxide 0.1 mg/50 mL
INACTIVE INGREDIENTS: Water; Propylene Glycol

ACTIVE INGREDIENT

Active Ingredient: Titanium Dioxide 5.0%, Zinc Oxide 0.2%

INACTIVE INGREDIENT

Inactive Ingredients: Water, Cetyl Ethylhexanoate, Caprylic/Capric Triglyceride, Propylene Glycol, Cetyl PEG/PPG-10/1 Dimethicone, 1,2-Hexanediol, Zinc Stearate, Silica Dimethyl Silylate, Linum Usitatissimum (Linseed) Seed Oil, Magnesium Sulfate, Sodium Hyaluronate, Sorbitan Sesquioleate, Hydroxyethylcellulose, Pichia Anomala Extract, Yeast Extract, Hydrolyzed Myrtus Communis Leaf Extract, Undaria Pinnatifida Extract, Myrothamnus Flabellifolia Callus Culture Extract, Pentylene Glycol, Lactuca Indica Extract, Corydalis Ochotensis Extract, Draba Nemorosa Extract, Chenopodium Album Flower Extract, Lactobacillus/Soybean Ferment Extract, Salix Alba (Willow) Bark Extract, Cinnamomum Cassia Bark Extract, Origanum Vulgare Leaf Extract, Chamaecyparis Obtusa Leaf Extract, Scutellaria Baicalensis Root Extract, Portulaca Oleracea Extract, Microcrystalline Wax, Allantoin, Beta-Glucan, Tocopheryl Acetate, Ultramarines, CI 77499, CI 77491, CI 77492

PURPOSE

Purpose: Sunscreen

WARNINGS

Warnings: 1. In case of having following symptoms after using this, you’re advised to stop using it immediately. If you keep using it, the symptoms will get worse and need to consult a dermatologist. 1) In case of having problems such as red rash, swollenness, itching, stimulation during usage. 2) In case of having the same symptoms above on the part you put this product on by direct sunlight. 2. You are banned to use it on the part where you have a scar, eczema, or dermatitis. 3. In case of getting it into your eyes, you have to wash it immediately.

KEEP OUT OF REACH OF CHILDREN

Keep out of reach of babies and children

DESCRIPTION

Indications & Usage: Apply a desired amount evenly over entire face.

Dosage & Administration: Take an adequate amount of this product.